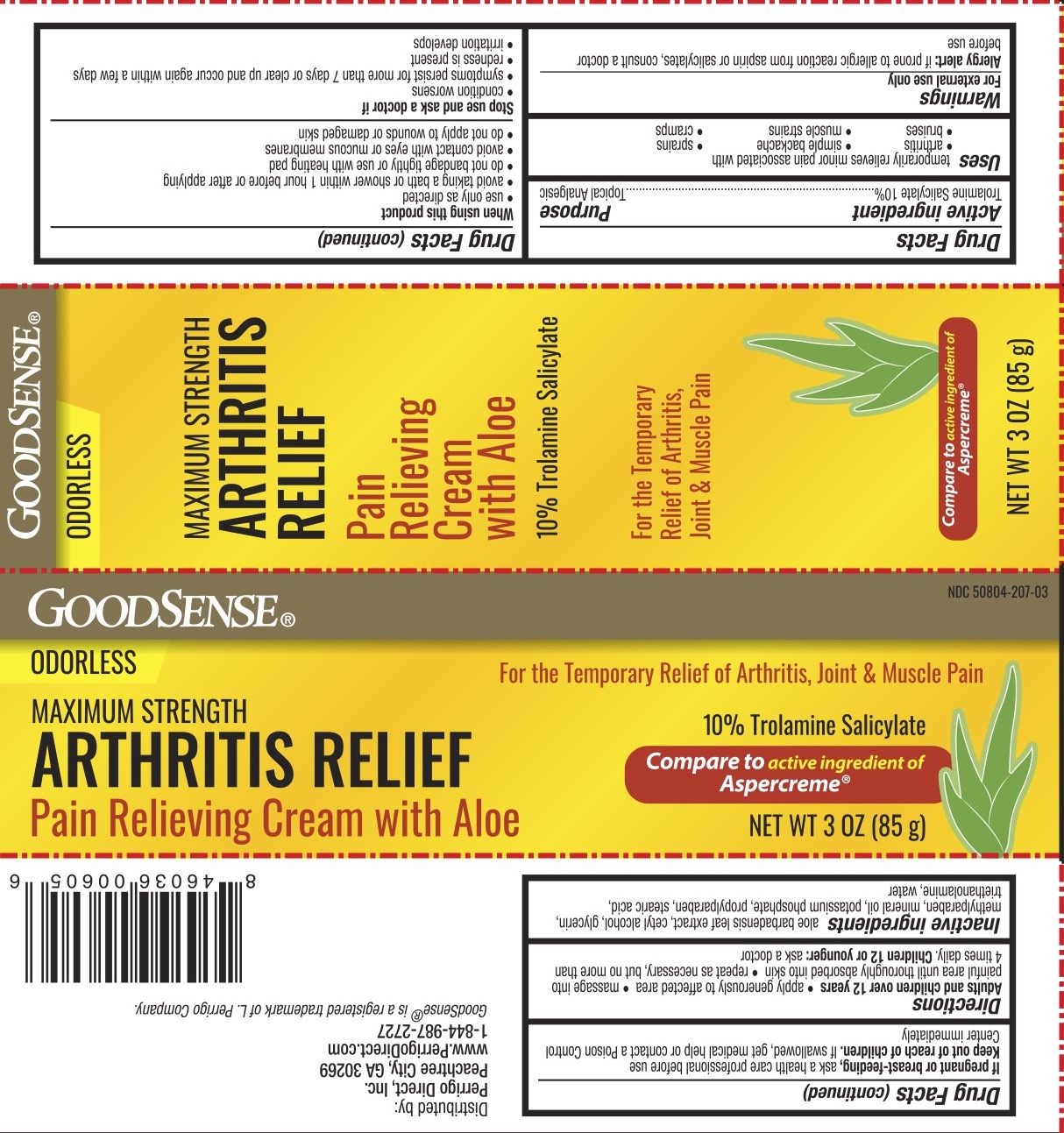 DRUG LABEL: Arthritis Relief
NDC: 50804-207 | Form: CREAM
Manufacturer: Geiss, Destin & Dunn, Inc
Category: otc | Type: HUMAN OTC DRUG LABEL
Date: 20200402

ACTIVE INGREDIENTS: TROLAMINE SALICYLATE 10 g/100 g
INACTIVE INGREDIENTS: WATER; ALOE VERA LEAF; CETYL ALCOHOL; METHYLPARABEN; POTASSIUM PHOSPHATE, MONOBASIC; PROPYLPARABEN; STEARIC ACID; GLYCERIN; TROLAMINE; MINERAL OIL

ACTIVE INGREDIENT

Trolamine Salicylate 10%

PURPOSE

Topical Analgesic

DOSAGE AND ADMINISTRATION

Temporarily relieves minor pain associated with arthritis, simple backache, muscle strain, sprains, bruises, cramps.

WARNINGS

For external use only.

Allergy Alert: If prone to allergic reaction from aspirin or salicylates, consult a doctor before use.

When using this product use only as directed, avoid taking a bath or shower within 1 hour before or after applying, do not bandage tightly or use with a heating pad, avoid contact with eyes or mucous membranes, do not apply to wounds or damaged skin.

Stop use and ask a doctor if condition worsens or symptoms persist for more than 7 days if symptoms clear up and occur again within a few days, or if redness or irritation develops.

PREGNANCY OR BREAST FEEDING

Ask a health-care professional before use.

Keep out of reach of children.

INDICATIONS AND USAGE

Adults and children over 12 years: apply generously to the affected area, massage into painful area until thoroughly absorbed into the skin, repeat as necessary, but no more than 4 times daily. Children under 12 years or younger: ask a doctor.

INACTIVE INGREDIENT

Acrylates/C10-30 Alkyl Acrylate Crosspolymer, Aminomethyl Propanol, Blue 1, Copper PCA, Ethyhexylglycerin, Eucalyptus Globulus Leaf Oil, Glycerin, Isopropyl Alcohol, Phenoxyethanol, Water.